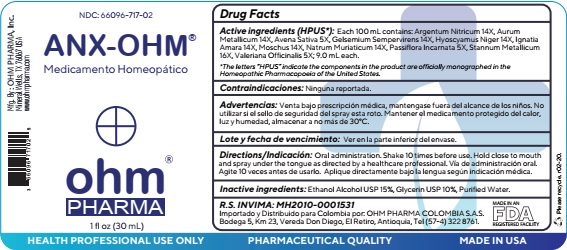 DRUG LABEL: OHM-ANX
NDC: 66096-717 | Form: SPRAY
Manufacturer: OHM PHARMA INC.
Category: homeopathic | Type: HUMAN OTC DRUG LABEL
Date: 20211115

ACTIVE INGREDIENTS: SILVER NITRATE 14 [hp_X]/30 mL; GOLD 14 [hp_X]/30 mL; AVENA SATIVA FLOWERING TOP 5 [hp_X]/30 mL; GELSEMIUM SEMPERVIRENS ROOT 14 [hp_X]/30 mL; HYOSCYAMUS NIGER 14 [hp_X]/30 mL; STRYCHNOS IGNATII SEED 14 [hp_X]/30 mL; MOSCHUS MOSCHIFERUS MUSK SAC RESIN 14 [hp_X]/30 mL; SODIUM CHLORIDE 14 [hp_X]/30 mL; PASSIFLORA INCARNATA FLOWERING TOP 5 [hp_X]/30 mL; TIN 16 [hp_X]/30 mL; VALERIAN 5 [hp_X]/30 mL
INACTIVE INGREDIENTS: ALCOHOL; GLYCERIN; WATER

OHM-ANX

ACTIVE INGREDIENT

Active ingredients (HPUS*): Each 100 mL contains: Argentum Nitricum 14X, Aurum
Metallicum 14X, Avena Sativa 5X, Gelsemium Sempervirens 14X, Hyoscyamus Niger 14X, Ignatia
Amara 14X, Moschus 14X, Natrum Muriaticum 14X, Passiflora Incarnata 5X, Stannum Metallicum
16X, Valeriana Officinalis 5X; 9.0 mL each.

*The letters “HPUS” indicate the components in the product are officially monographed in the
Homeopathic Pharmacopoeia of the United States.

INDICATIONS AND USAGE

Contraindicaciones: Ninguna reportada

WARNINGS

Advertencias: Venta bajo prescripción médica, mantengase fuera del alcance de los niños. No utilizar si el sello de seguridad del spray esta roto. Mantener el medicamento protegido del calor, luz y humedad, almacenar a no más de 30°C.

KEEP OUT OF REACH OF CHILDREN

Mantengase fuera del alcance de los niños.

DOSAGE AND ADMINISTRATION

Directions/Indicación: Oral administration. Shake 10 times before use. Hold close to mouth
and spray under the tongue as directed by a healthcare professional. Vía de administración oral.
Agite 10 veces antes de usarlo. Aplique directamente bajo la lengua según indicación médica.

INACTIVE INGREDIENT

Inactive ingredients: Ethanol Alcohol USP 15%, Glycerin USP 10%, Purified Water.

OTHER SAFETY INFORMATION

Lote y fecha de vencimiento: Ver en la parte inferior del envase

QUESTIONS

R.S. INVIMA: MH2010-0001591
Importado y Distribuido para Colombia por: OHM PHARMA COLOMBIA S.A.S.
Bodega 5, Km 23, Vereda Don Diego, El Retiro, Antioquia, Tel (57-4) 322 8761.

Mfg. By : OHM PHARMA, Inc.
Mineral Wells, TX 76067 USA
www.ohmpharma.com

PACKAGE LABEL

NDC: 66096-717-02

ANX-OHM

Medicamento Homeopático

ohm

PHARMA

1 fl oz (30 mL)

PURPOSE

Medicamento Homeopático